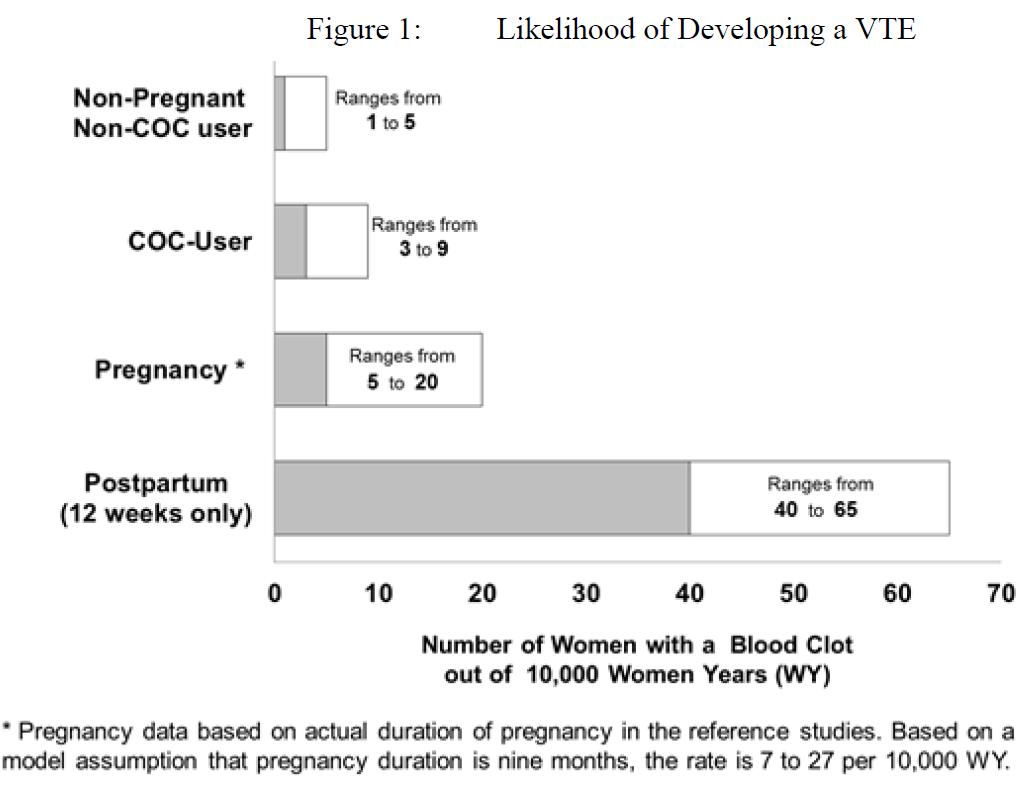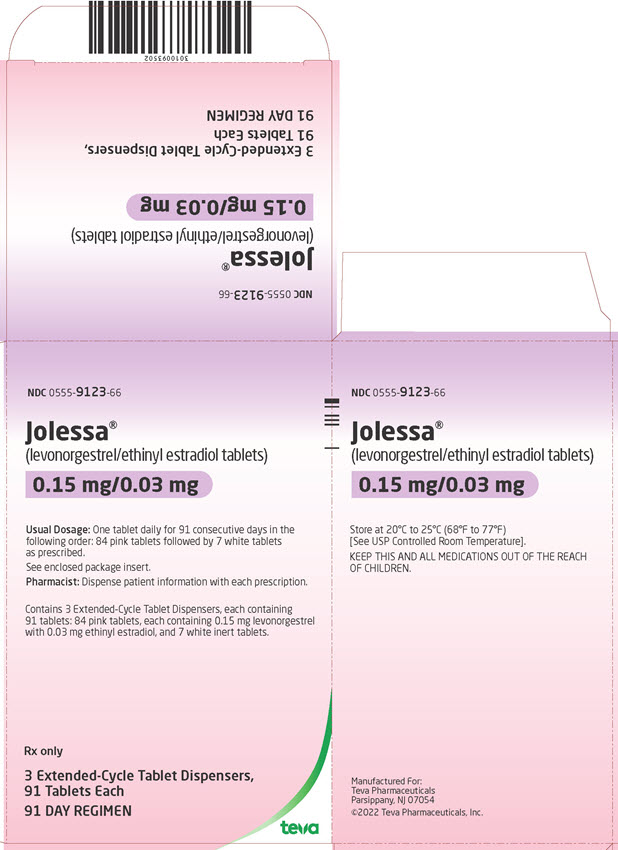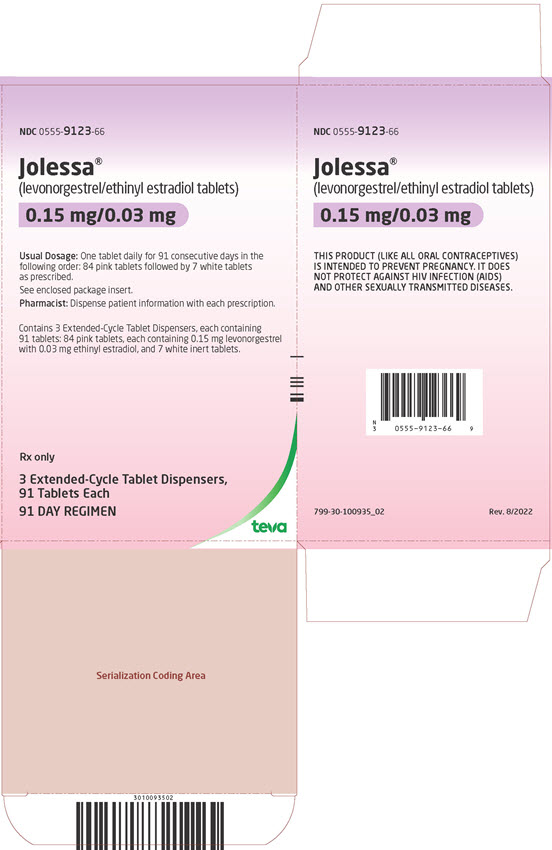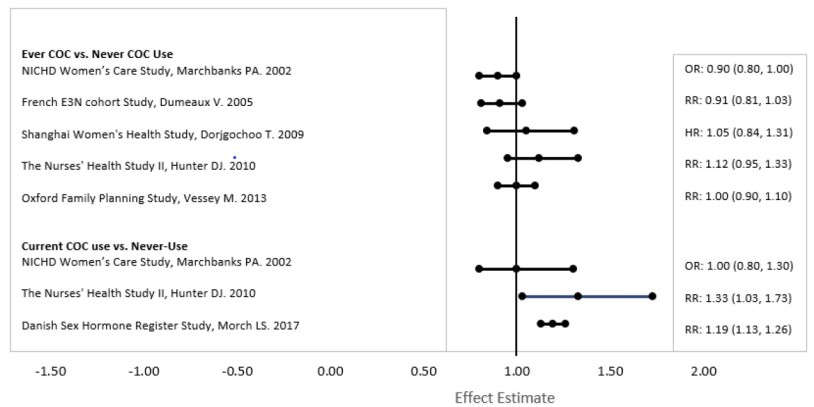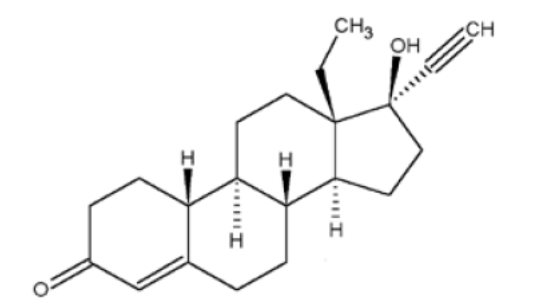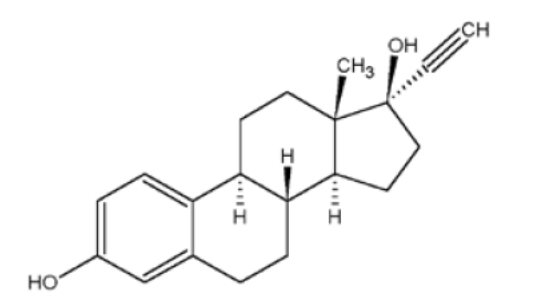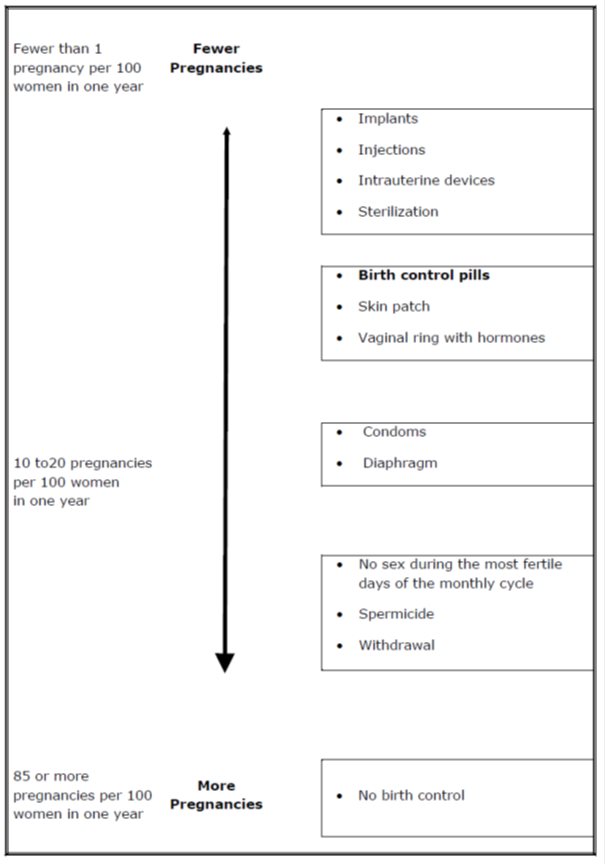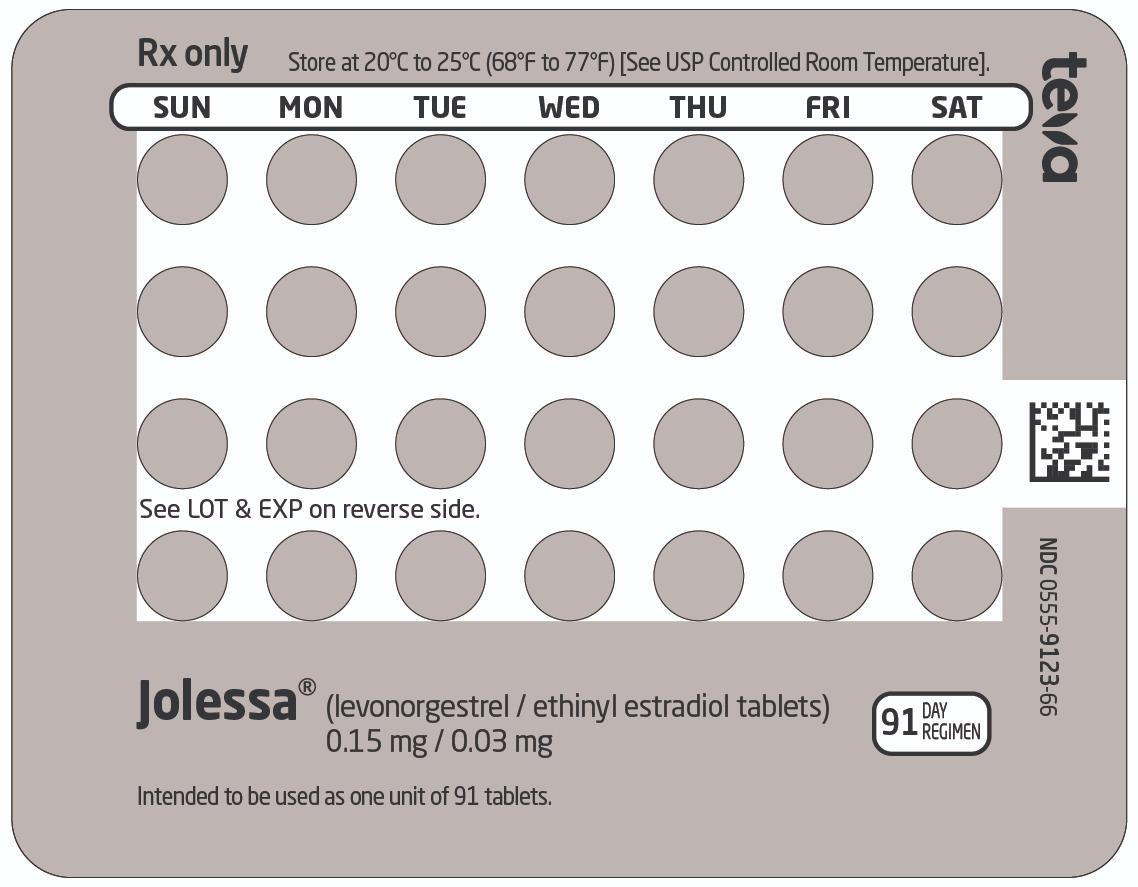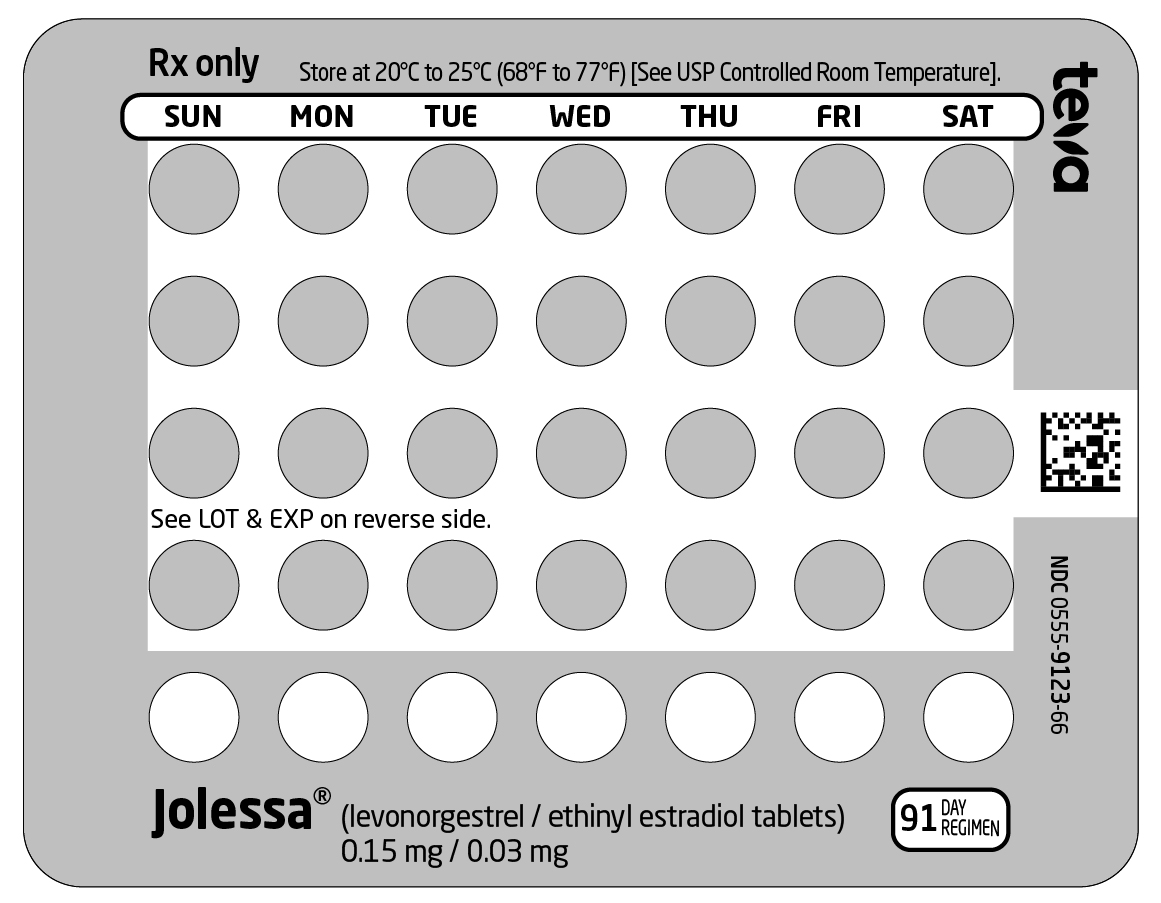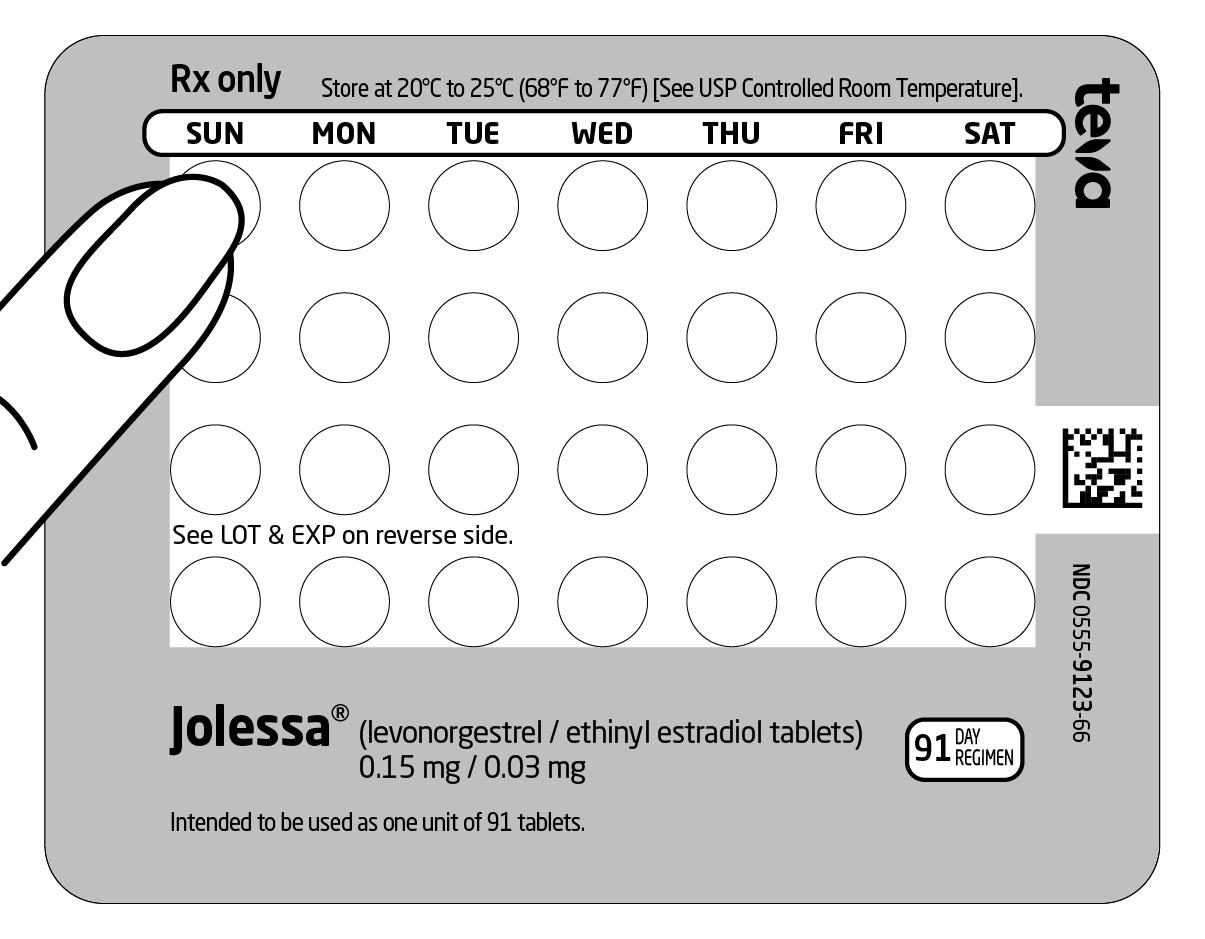 DRUG LABEL: Jolessa
NDC: 0555-9123 | Form: KIT | Route: ORAL
Manufacturer: Teva Pharmaceuticals USA, Inc.
Category: prescription | Type: HUMAN PRESCRIPTION DRUG LABEL
Date: 20241024

ACTIVE INGREDIENTS: LEVONORGESTREL 0.15 mg/1 1; ETHINYL ESTRADIOL 0.03 mg/1 1
INACTIVE INGREDIENTS: ANHYDROUS LACTOSE; FD&C BLUE NO. 1; FD&C RED NO. 40; HYPROMELLOSE 2208 (3 MPA.S); HYPROMELLOSE 2910 (3 MPA.S); HYPROMELLOSE 2910 (6 MPA.S); MICROCRYSTALLINE CELLULOSE; POLYETHYLENE GLYCOL 400; MAGNESIUM STEARATE; POLYSORBATE 80; TITANIUM DIOXIDE; ANHYDROUS LACTOSE; HYPROMELLOSE 2208 (3 MPA.S); MICROCRYSTALLINE CELLULOSE; MAGNESIUM STEARATE

HIGHLIGHTS OF PRESCRIBING INFORMATION

These highlights do not include all the information needed to use JOLESSA safely and effectively. See full prescribing information for JOLESSA.
JOLESSA® (levonorgestrel and ethinyl estradiol tablets) for oral use
Initial U.S. Approval: 1982

WARNING: CIGARETTE SMOKING AND SERIOUS CARDIOVASCULAR EVENTS

See full prescribing information for complete boxed warning.

- JOLESSA is contraindicated in women over 35 years old who smoke. (4)
- Cigarette smoking increases the risk of serious cardiovascular events from combination oral contraceptive (COC) use. (5.1)

1 INDICATIONS AND USAGE

JOLESSA is a combination of levonorgestrel, a progestin, and ethinyl estradiol, an estrogen, indicated for use by females of reproductive potential to prevent pregnancy. (1)

2 DOSAGE AND ADMINISTRATION

- Take one tablet daily by mouth at the same time every day for 91 days. (2.1)
- Take tablets in the order directed on the Extended-Cycle Tablet Dispenser. (2.2)

3 DOSAGE FORMS AND STRENGTHS

JOLESSA consists of 84 round, pink tablets containing 0.15 mg of levonorgestrel and 0.03 mg of ethinyl estradiol, and 7 round, white inert tablets. (3)

4 CONTRAINDICATIONS

- A high risk of arterial or venous thrombotic diseases (4)
- Liver tumors or liver disease, acute viral hepatitis or decompensated cirrhosis (4)
- Undiagnosed abnormal uterine bleeding (4)
- Breast cancer (4)
- Co-administration with Hepatitis C drug combinations containing ombitasvir/paritaprevir/ritonavir, with or without dasabuvir. (4)

5 WARNINGS AND PRECAUTIONS

- Vascular risks: Stop if a thrombotic or thromboembolic event occurs. Stop at least 4 weeks before and through 2 weeks after major surgery. Start no earlier than 4 weeks after delivery, in women who are not breastfeeding. Consider cardiovascular risk factors before initiating in all females, particularly those over 35 years. (5.1, 5.5)
- Liver disease: Discontinue if jaundice occurs. (5.2)
- Hypertension: If used in women with well-controlled hypertension, monitor blood pressure and stop if blood pressure rises significantly. (5.4)
- Gallbladder disease: May cause or worsen gallbladder disease. (5.6)
- Adverse carbohydrate and lipid effects: Monitor glucose in prediabetic and diabetic women taking JOLESSA. Consider an alternate contraceptive method for women with uncontrolled dyslipidemia. (5.7)
- Headache: Evaluate significant change in headaches and discontinue if indicated. (5.8)
- Uterine bleeding: May cause irregular bleeding or amenorrhea. Evaluate for other causes if symptoms persist. (5.9)

6 ADVERSE REACTIONS

The most common adverse reactions (≥2%) reported during clinical trials were headache, menorrhagia, nausea, dysmenorrhea, acne, migraine, breast tenderness, weight increased, and depression. (6.1)

To report SUSPECTED ADVERSE REACTIONS, contact Teva Pharmaceuticals at 1-888-483-8279 or FDA at 1-800-FDA-1088 or www.fda.gov/medwatch.

7 DRUG INTERACTIONS

Enzyme inducers (e.g. CYP3A4): May decrease the effectiveness of JOLESSA or increase breakthrough bleeding. Counsel patients to use a backup or alternative method of contraception when enzyme inducers are used with JOLESSA. (7.1)

8 USE IN SPECIFIC POPULATIONS

- Pregnancy: Discontinue if pregnancy occurs. (8.1)
- Lactation: Advise use of another contraceptive method; JOLESSA can decrease milk production. (8.2)

FULL PRESCRIBING INFORMATION

WARNING: CIGARETTE SMOKING AND SERIOUS CARDIOVASCULAR EVENTS

Cigarette smoking increases the risk of serious cardiovascular events from combination oral contraceptive (COC) use. This risk increases with age, particularly in women over 35 years of age, and with the number of cigarettes smoked. For this reason, COCs, including JOLESSA, are contraindicated in women who are over 35 years of age and smoke [see Contraindications (4) and Warnings and Precautions (5.1)].

1 INDICATIONS AND USAGE

JOLESSA® is indicated for use by females of reproductive potential to prevent pregnancy.

2 DOSAGE AND ADMINISTRATION

2.1 How to Start and Take JOLESSA

JOLESSA is dispensed in an Extended-Cycle Tablet Dispenser [see How Supplied/Storage and Handling (16)]. JOLESSA should be started on a Sunday (see Table 1). For the first cycle of a Sunday Start regimen, an additional method of contraception should be used until after the first 7 consecutive days of administration.

Table 1: Instructions for Administration of JOLESSA

Starting JOLESSA in females with no current use of hormonal contraception (Sunday Start); Important:; Consider the possibility of ovulation and conception prior to initiation of this product.; Tablet Color:; - JOLESSA active tablets are pink (Day 1 to Day 84). - JOLESSA inactive tablets are white (Day 85 to Day 91). | Sunday Start:; For each 91-day course, take in the following order:; - Take the first pink tablet (0.15 mg of levonorgestrel and 0.03 mg ethinyl estradiol) on the first Sunday after the onset of menstruation. If menstruation begins on a Sunday, take the tablet on that day. Due to the potential risk of becoming pregnant, use additional non-hormonal contraception (such as condoms or spermicide) for the first 7 days of treatment. - Take subsequent pink tablets once daily at the same time each day for a total of 84 days. - Take one white tablet (inert) daily for the following 7 days and at the same time of day that active tablets were taken. A scheduled period should occur during the 7 days that the white tablets are taken. - Begin the next and all subsequent 91-day courses of JOLESSA without interruption on the same day of the week (Sunday) on which the patient began her first dose. Follow the same schedule as the initial 91-day course: a pink tablet once a day for 84 days, and a white tablet once a day for 7 days. If the patient does not immediately start her next pill pack, instruct her to protect herself from pregnancy by using a non-hormonal backup method of contraception until she has taken a pink tablet daily for 7 consecutive days.
Switching from another contraceptive method to JOLESSA | Start JOLESSA:
Another oral contraceptive | On the day when the new pack of the previous COC would have been started
Transdermal patch | On the day when the next application would have been scheduled.
Vaginal ring | On the day when the next insertion would have been scheduled.
Injection | On the day when the next injection would have been scheduled.
Intrauterine contraceptive (IUD) | - On the day of removal. - If the IUD is not removed on first day of the patient’s menstrual cycle, additional non-hormonal contraception (such as condoms or spermicide) is needed for the first seven days of the first 91-day course.
Implant | On the day of removal.

Starting JOLESSA after Abortion or Miscarriage

First-trimester

- After a first-trimester abortion or miscarriage, JOLESSA may be started immediately. An additional method of contraception is not needed if JOLESSA is started immediately.
- If JOLESSA is not started within 5 days after termination of the pregnancy, the patient should use additional non-hormonal contraception (such as condoms or spermicide) for the first seven days of her first 91-day course of JOLESSA.

Second-trimester

- Do not start JOLESSA until 4 weeks after a second-trimester abortion or miscarriage, due to the increased risk of thromboembolic disease. Start JOLESSA following the instructions in Table 1 for Sunday start. Use additional non-hormonal contraception (such as condoms or spermicide) for the first seven days of the patient’s first 91-day course of JOLESSA [see Contraindications (4), Warnings and Precautions (5.1)].

Starting JOLESSA after Childbirth

- Do not start JOLESSA until 4 weeks after delivery, due to the increased risk of thromboembolic disease. Start contraceptive therapy with JOLESSA following the instructions in Table 1 for women not currently using hormonal contraception.
- JOLESSA is not recommended for use in lactating women [see Use in Specific Populations (8.2)].
- If the woman has not yet had a period postpartum, consider the possibility of ovulation and conception occurring prior to use of JOLESSA [see Contraindications (4), Warnings and Precautions (5.1), Use in Specific Populations (8.1 and 8.2)].

2.2 Dosing JOLESSA

Instruct patients to take one tablet by mouth at the same time every day. The dosing of JOLESSA is one pink pill containing levonorgestrel and ethinyl estradiol daily for 84 consecutive days, followed by one white pill (inactive pills without hormone) for 7 days. To achieve maximum contraceptive effectiveness, JOLESSA must be taken exactly as directed, in the order directed on the Tablet Dispenser, and at intervals not exceeding 24 hours. Start taking the first pink pill from a new Tablet Dispenser the very next day after taking the last white inactive pill in the Tablet Dispenser. The failure rate may increase when pills are missed or taken incorrectly.

2.3 Missed Doses

Table 2: Instructions for Missed JOLESSA Tablets

- If one active tablet (pink) is missed in Days 1 through 84 | Take the tablet as soon as possible. Take the next tablet at the regular time and continue taking one tablet a day until the 91-day course is finished.
- If two consecutive active tablets (pink) are missed in Days 1 through 84 | Take 2 tablets on the day remembered and 2 tablets the next day. Then continue taking one tablet a day until the 91-day course is finished. Additional non-hormonal contraception (such as condoms or spermicide) should be used as backup if the patient has sex within 7 days after missing tablets.
- If three or more consecutive active tablets (pink) are missed in Days 1 through 84 | Do not take the missed tablets. Continue taking one tablet a day until the 91-day course is finished. Additional non-hormonal contraception (such as condoms or spermicide) must be used as backup if the patient has sex within 7 days after missing tablets.
- If any of the seven white (inactive) tablets are missed | Throw away the missed tablets. Continue taking the remaining tablets until the pack is finished. A backup birth control method is not needed.

2.4 Advice in Case of Gastrointestinal Disturbances

In case of severe vomiting or diarrhea, absorption may not be complete and additional contraceptive measures should be taken. If vomiting or diarrhea occurs within 3-4 hours after taking a pink tablet, handle this as a missed tablet.

3 DOSAGE FORMS AND STRENGTHS

JOLESSA (levonorgestrel and ethinyl estradiol tablets) are available as round, film-coated, biconvex, unscored tablets with a debossed stylized b on one side, packaged in Extended-Cycle Tablet Dispensers, each containing a 13-week supply of tablets in the following order:

- 84 pink tablets, each containing 0.15 mg of levonorgestrel and 0.03 mg ethinyl estradiol; debossed with 992 on the other side
- 7 white inert tablets debossed with 208 on the other side.

4 CONTRAINDICATIONS

JOLESSA is contraindicated in females who are known to have or develop the following conditions:

- A high risk of arterial or venous thrombotic diseases. Examples include females who are known to:

- Smoke, if over age 35 [see Boxed Warning and Warnings and Precautions (5.1)].
- Have current or history of deep vein thrombosis or pulmonary embolism [see Warnings and Precautions (5.1)].
- Have cerebrovascular disease [see Warnings and Precautions (5.1)].
- Have coronary artery disease [see Warnings and Precautions (5.1)].
- Have thrombogenic valvular or thrombogenic rhythm diseases of the heart (for example, subacute bacterial endocarditis with valvular disease, or atrial fibrillation) [see Warnings and Precautions (5.1)].
- Have inherited or acquired hypercoagulopathies [see Warnings and Precautions (5.1)].
- Have uncontrolled hypertension or hypertension with vascular disease [see Warnings and Precautions (5.4)].
- Have diabetes mellitus and are over age of 35, diabetes mellitus with hypertension or vascular disease or other end-organ damage, or diabetes mellitus of >20 years duration [see Warnings and Precautions (5.7)].
- Have headaches with focal neurological symptoms, migraine headaches with aura, or over age 35 with any migraine headaches [see Warnings and Precautions (5.8)].

- Current diagnosis of, or history of breast cancer, which may be hormone sensitive [see Warnings and Precautions (5.11)].
- Liver tumors, acute viral hepatitis, or severe (decompensated) cirrhosis [see Warnings and Precautions (5.2) and Use in Specific Populations (8.6)].
- Undiagnosed abnormal uterine bleeding [see Warnings and Precautions (5.9)].
- Use of Hepatitis C drug combinations containing ombitasvir/paritaprevir/ritonavir, with or without dasabuvir, due to the potential for ALT elevations [see Warnings and Precautions (5.3)].

5 WARNINGS AND PRECAUTIONS

5.1 Thromboembolic Disorders and Other Vascular Conditions

- Stop JOLESSA if an arterial or venous thrombotic/thromboembolic event occurs.
- Stop JOLESSA if there is unexplained loss of vision, proptosis, diplopia, papilledema, or retinal vascular lesions. Evaluate for retinal vein thrombosis immediately.
- Discontinue JOLESSA during prolonged immobilization. If feasible, stop JOLESSA at least 4 weeks before and through 2 weeks after major surgery or other surgeries known to have an elevated risk of thromboembolism.
- Start JOLESSA no earlier than 4 weeks after delivery in females who are not breastfeeding. The risk of postpartum thromboembolism decreases after the third postpartum week, whereas the likelihood of ovulation increases after the third postpartum week.
- Before starting JOLESSA evaluate any past medical history or family history of thrombotic or thromboembolic disorders and consider whether the history suggests an inherited or acquired hypercoagulopathy. JOLESSA is contraindicated in females with a high risk of arterial or venous thrombotic/thromboembolic diseases [see Contraindications (4)].

Arterial Events

COCs increase the risk of cardiovascular events and cerebrovascular events, such as myocardial infarction and stroke. The risk is greater among older women (> 35 years of age), smokers, and females with hypertension, dyslipidemia, diabetes, or obesity.

JOLESSA is contraindicated in women over 35 years of age who smoke [see Contraindications (4)]. Cigarette smoking increases the risk of serious cardiovascular events from COC use. This risk increases with age, particularly in women over 35 years of age, and with the number of cigarettes smoked.

Venous Events

Use of COCs increases the risk of venous thromboembolic events (VTEs), such as deep vein thrombosis and pulmonary embolism. Risk factors for VTEs include smoking, obesity, and family history of VTE, in addition to other factors that contraindicate use of COCs [see Contraindications (4)]. While the increased risk of VTE associated with use of COCs is well-established, the rates of VTE are even greater during pregnancy, and especially during the postpartum period (see Figure 1). The rate of VTE in females using COCs has been estimated to be 3 to 9 cases per 10,000 woman years.

The risk of VTE is highest during the first year of use of a COC and when restarting hormonal contraception after a break of four weeks or longer. The risk of thromboembolic disease due to COCs gradually disappears after COC use is discontinued.

Figure 1 shows the risk of developing a VTE for females who are not pregnant and do not use oral contraceptives, for females who use oral contraceptives, for pregnant females and for females in the postpartum period. To put the risk of developing a VTE into perspective: If 10,000 females who are not pregnant and do not use oral contraceptives are followed for one year, between 1 and 5 of these females will develop a VTE.

Use of JOLESSA provides women with more hormonal exposure on a yearly basis than conventional monthly COCs containing the same strength synthetic estrogens and progestins (an additional 9 weeks of exposure per year). In the clinical trial, one case of pulmonary embolism was reported. Postmarketing adverse reactions of VTE have been reported in women who used JOLESSA.

5.2 Liver Disease

Elevated Liver Enzymes

JOLESSA is contraindicated in females with acute viral hepatitis or severe (decompensated) cirrhosis of the liver [see Contraindications (4)]. Acute liver test abnormalities may necessitate the discontinuation of JOLESSA until the liver tests return to normal and JOLESSA causation has been excluded. Discontinue JOLESSA if jaundice develops.

Liver Tumors

JOLESSA is contraindicated in females with benign and malignant liver tumors [see Contraindications (4)]. COCs increase the risk of hepatic adenomas. An estimate of the attributable risk is 3.3 cases/100,000 COC users. Rupture of hepatic adenomas may cause death through intra-abdominal hemorrhage.

Studies have shown an increased risk of developing hepatocellular carcinoma in long-term (>8 years) COC users. The attributable risk of liver cancers in COC users is less than one case per million users.

5.3 Risk of Liver Enzyme Elevations with Concomitant Hepatitis C Treatment

During clinical trials with the Hepatitis C combination drug regimen that contains ombitasvir/paritaprevir/ritonavir, with or without dasabuvir, ALT elevations greater than 5 times the upper limit of normal (ULN), including some cases greater than 20 times the ULN, were significantly more frequent in women using ethinyl estradiol-containing medications, such as JOLESSA. Discontinue JOLESSA prior to starting therapy with the combination drug regimen ombitasvir/paritaprevir/ritonavir, with or without dasabuvir [see Contraindications (4)]. JOLESSA can be restarted approximately 2 weeks following completion of treatment with the Hepatitis C combination drug regimen.

5.4 Hypertension

JOLESSA is contraindicated in females with uncontrolled hypertension or hypertension with vascular disease [see Contraindications (4)]. For all women, including those with well-controlled hypertension, monitor blood pressure at routine visits and stop JOLESSA if blood pressure rises significantly.

An increase in blood pressure has been reported in females taking COCs, and this increase is more likely in older women and with extended duration of use. The effect of COCs on blood pressure may vary according to the progestin in the COC.

5.5 Age-related Considerations

The risk for cardiovascular disease and prevalence of risk factors for cardiovascular disease increase with age. Certain conditions, such as smoking and migraine headache without aura, that do not contraindicate COC use in younger females, are contraindications to use in women over 35 years of age [see Contraindications (4) and Warnings and Precautions (5.1)]. Consider the presence of underlying risk factors that may increase the risk of cardiovascular disease or VTE, particularly before initiating JOLESSA for women over 35 years, such as:

- Hypertension
- Diabetes
- Dyslipidemia
- Obesity

5.6 Gallbladder Disease

Studies suggest a small increased relative risk of developing gallbladder disease among COC users. Use of COCs, including JOLESSA, may worsen existing gallbladder disease.

A past history of COC-related cholestasis predicts an increased risk with subsequent COC use. Females with a history of pregnancy-related cholestasis may be at an increased risk for COC-related cholestasis.

5.7 Adverse Carbohydrate and Lipid Metabolic Effects

Hyperglycemia

JOLESSA is contraindicated in diabetic women over age 35, or females who have diabetes with hypertension, nephropathy, retinopathy, neuropathy, other vascular disease or females with diabetes of >20 years of duration [see Contraindications (4)]. JOLESSA may decrease glucose tolerance. Carefully monitor prediabetic and diabetic females who are using JOLESSA.

Dyslipidemia

Consider alternative contraception for females with uncontrolled dyslipidemia. JOLESSA may cause adverse lipid changes.

Females with hypertriglyceridemia, or a family history thereof, may have an increase in serum triglyceride concentrations when using JOLESSA, which may increase the risk of pancreatitis.

5.8 Headache

JOLESSA is contraindicated in females who have headaches with focal neurological symptoms or have migraine headaches with aura, and in women over age 35 years who have migraine headaches with or without aura [see Contraindications (4)].

If a female taking JOLESSA develops new headaches that are recurrent, persistent, or severe, evaluate the cause and discontinue JOLESSA if indicated. Consider discontinuation of JOLESSA if there is an increased frequency or severity of migraine during COC use (which may be prodromal of a cerebrovascular event) [see Contraindications (4)].

5.9 Bleeding Irregularities and Amenorrhea

Bleeding and/or spotting that occurs at any time while taking the first 84 tablets of each extended-cycle regimen is considered “unscheduled” bleeding/spotting. Bleeding that occurs during the time a woman takes the seven white inert tablets is considered “scheduled” bleeding.

Unscheduled Bleeding and Spotting

Females using JOLESSA may experience unscheduled (breakthrough or intracyclic) bleeding and spotting especially during the first 3 months of use. Bleeding irregularities may resolve over time or by changing to a different contraceptive product. If unscheduled bleeding persists or occurs after previously regular cycles, evaluate for causes such as pregnancy or malignancy.

Before prescribing JOLESSA, advise the woman to weigh the occurrence of fewer scheduled menses (4 per year instead of 13 per year) against the occurrence of increased unscheduled bleeding and/or spotting.

The clinical trial of the efficacy of JOLESSA (91-day cycles) in preventing pregnancy also assessed scheduled and unscheduled bleeding. The participants in the study were composed primarily of women who had used oral contraceptives previously as opposed to new users. Women with a history of breakthrough bleeding/spotting ≥ 10 consecutive days on oral contraceptives were excluded from the study. More JOLESSA subjects, compared to subjects on the comparator 28-day cycle regimen, discontinued prematurely for unacceptable bleeding (7.7% [JOLESSA] vs. 1.8% [28-day cycle regimen]).

Unscheduled bleeding and unscheduled spotting decreased over successive 91-day cycles. Table 3 below presents the number of days with unscheduled bleeding and/or spotting for each respective 91-day cycle.

Table 3: Number of Unscheduled Bleeding and/or Spotting Days per 91-day Cycle

Cycle (N) | Days of Unscheduled Bleeding and/or Spotting per 84-Day Interval |  |  |  | Median Days Per Subject-Month
Cycle (N) | Mean | Q1 | Median | Q3 | Median Days Per Subject-Month
1 (446) | 15.1 | 3.0 | 12 | 23.0 | 3.0
2 (368) | 11.6 | 2.0 | 6 | 17.5 | 1.5
3 (309) | 10.6 | 1.0 | 6 | 15.0 | 1.5
4 (282) | 8.8 | 1.0 | 4 | 14.0 | 1.0

Q1=Quartile 1: 25% of women had ≤ this number of days of unscheduled bleeding/spotting

Median: 50% of women had ≤ this number of days of unscheduled bleeding/spotting

Q3=Quartile 3: 75% of women had ≤ this number of days of unscheduled bleeding/spotting

Table 4 shows the percentages of women with ≥7 days and ≥20 days of unscheduled spotting and/or bleeding in the JOLESSA and the 28-day cycle treatment groups.

Table 4: Percentage of Subjects with Unscheduled Bleeding and/or Spotting

Days of unscheduled bleeding and/or spotting | Percentage of Subjects a
JOLESSA | Cycle 1 (N=385) | Cycle 4 (N=261)
≥ 7 days | 65% | 42%
≥ 20 days | 35% | 15%
28-day regimen | Cycles 1-4 (N=194) | Cycles 10-13 (N=158)
≥ 7 days | 38% | 39%
≥ 20 days | 6% | 4%

a Based on spotting and/or bleeding on days 1-84 of a 91 day cycle in the JOLESSA subjects and days 1-21 of a 28 day cycle over 4 cycles in the 28-day dosing regimen.

Total days of bleeding and/or spotting (scheduled plus unscheduled) were similar over one year of treatment for JOLESSA subjects and subjects on the 28-day cycle regimen.

Amenorrhea and Oligomenorrhea

Females who use JOLESSA may experience absence of scheduled (withdrawal) bleeding, even if they are not pregnant. Based on data from the clinical trial of JOLESSA, amenorrhea occurred in approximately 0.8% of females during Cycle 1, 1.2% of females during Cycle 2, 3.7% of females during Cycle 3, and 3.4% of females during Cycle 4.

Because females using JOLESSA will likely have scheduled bleeding only 4 times per year, rule out pregnancy at the time of any missed menstrual period.

After discontinuation of JOLESSA, amenorrhea or oligomenorrhea may occur, especially if these conditions were pre-existent.

5.10 Depression

Carefully observe females with a history of depression and discontinue JOLESSA if depression recurs to a serious degree. Data on the association of COCs with onset of depression or exacerbation of existing depression are limited.

5.11 Malignant Neoplasms

Breast Cancer

JOLESSA is contraindicated in females who currently have or have had breast cancer because breast cancer may be hormonally sensitive [see Contraindications (4)].

Epidemiology studies have not found a consistent association between use of combined oral contraceptives (COCs) and breast cancer risk. Studies do not show an association between ever (current or past) use of COCs and risk of breast cancer. However, some studies report a small increase in the risk of breast cancer among current or recent users (<6 months since last use) and current users with longer duration of COC use [see Postmarketing Experience (6.2)].

Cervical Cancer

Some studies suggest that COC are associated with an increase in the risk of cervical cancer or intraepithelial neoplasia. However, there is controversy about the extent to which such findings may be due to differences in sexual behavior and other factors.

5.12 Effect on Binding Globulins

The estrogen component of JOLESSA may raise the serum concentrations of thyroxine-binding globulin, sex hormone-binding globulin and cortisol-binding globulin. The dose of replacement thyroid hormone or cortisol therapy may need to be increased.

5.13 Hereditary Angioedema

In females with hereditary angioedema, exogenous estrogens, including JOLESSA, may induce or exacerbate symptoms of hereditary angioedema.

5.14 Chloasma

Chloasma may occur with JOLESSA use, especially in females with a history of chloasma gravidarum. Advise females with a history of chloasma to avoid exposure to the sun or ultraviolet radiation while taking JOLESSA.

6 ADVERSE REACTIONS

The following serious adverse reactions with the use of COCs are discussed elsewhere in the labeling:

- Serious cardiovascular events and stroke [see Boxed Warning and Warnings and Precautions (5.1)]
- Vascular events [see Warnings and Precautions (5.1)]
- Liver disease [see Warnings and Precautions (5.2)]

6.1 Clinical Trial Experience

Because clinical trials are conducted under widely varying conditions, adverse reaction rates observed in the clinical trials of a drug cannot be directly compared to the rates in the clinical trials of another drug and may not reflect the rates observed in clinical practice.

The clinical trial that evaluated the safety and efficacy of JOLESSA was a 12-month, randomized, multicenter, open-label study, which enrolled women aged 18 to 40, of whom 456 took at least one dose of JOLESSA (345.14 woman-years of exposure) [see Clinical Studies (14)].

Adverse Reactions Leading to Study Discontinuation: 14.9% of the women discontinued from the clinical trial due to an adverse reaction; the most common adverse reactions (≥ 1% of women) leading to discontinuation in the JOLESSA group were menorrhagia (5.7%), mood swings (1.9%), weight/appetite increase (1.5%), and acne (1.3%).

Common Adverse Reactions (≥ 2% of women): headache (20.6%), menorrhagia (11.6%), nausea (7.5%), dysmenorrhea (5.7%), acne (4.6%), migraine (4.4%), breast tenderness (3.5%), weight increased (3.1%), and depression (2.1%).

Serious Adverse Reactions: pulmonary embolus, cholecystitis.

6.2 Postmarketing Experience

Five studies that compared breast cancer risk between ever-users (current or past use) of COCs and never-users of COCs reported no association between ever use of COCs and breast cancer risk, with effect estimates ranging from 0.90 - 1.12 (Figure 2).

Three studies compared breast cancer risk between current or recent COC users (<6 months since last use) and never users of COCs (Figure 2). One of these studies reported no association between breast cancer risk and COC use. The other two studies found an increased relative risk of 1.19 - 1.33 with current or recent use. Both of these studies found an increased risk of breast cancer with current use of longer duration, with relative risks ranging from 1.03 with less than one year of COC use to approximately 1.4 with more than 8-10 years of COC use.

Figure 2: Relevant Studies of Risk of Breast Cancer with Combined Oral Contraceptives

RR = relative risk; OR = odds ratio; HR = hazard ratio. “ever COC” are females with current or past COC use; “never COC use” are females that never used COCs.

The following adverse reactions have been identified during post-approval use of JOLESSA. Because these reactions are reported voluntarily from a population of uncertain size, it is not possible to reliably estimate their frequency or establish a causal relationship to drug exposure.

Gastrointestinal disorders: abdominal distension, vomiting

General disorders and administration site conditions: chest pain, fatigue, malaise, edema peripheral, pain

Immune system disorder: hypersensitivity reactions, including itching, rash, and angioedema

Investigations: blood pressure increased

Musculoskeletal and connective tissue disorders: muscle spasms, pain in extremity

Nervous system disorders: dizziness, loss of consciousness

Psychiatric disorders: insomnia

Reproductive and breast disorders: dysmenorrhea

Skin and subcutaneous tissue disorders: alopecia

Vascular disorders: thrombosis, pulmonary embolism, pulmonary thrombosis

7 DRUG INTERACTIONS

The sections below provide information on substances for which data on drug interactions with COCs are available. There is little information available about the clinical effect of most drug interactions that may affect COCs. However, based on the known pharmacokinetic effects of these drugs, clinical strategies to minimize any potential adverse effect on contraceptive effectiveness or safety are suggested.

Consult the approved product labeling of all concurrently used drugs to obtain further information about interactions with COCs or the potential for metabolic enzyme or transporter system alterations.

No drug-drug interaction studies were conducted with JOLESSA.

7.1 Effects of Other Drugs on Combined Oral Contraceptives

Substances decreasing the plasma concentrations of COCs and potentially diminishing the efficacy of COCs:

Table 5 includes substances that demonstrated an important drug interaction with JOLESSA.

Table 5: Significant Drug Interactions Involving Substances That Affect COCs

Metabolic Enzyme Inducers
Clinical effect | - Concomitant use of COCs with metabolic enzyme inducers may decrease the plasma concentrations of the estrogen and/or progestin component of COCs. - Decreased exposure of the estrogen and/or progestin component of COCs may potentially diminish the effectiveness of COCs and may lead to contraceptive failure or an increase in breakthrough bleeding.
Prevention or management | - Counsel females to use an alternative method of contraception or a backup method when enzyme inducers are used with COCs. - Continue backup contraception for 28 days after discontinuing the enzyme inducer to maintain contraceptive reliability.
Examples | Aprepitant, barbiturates, bosentan, carbamazepine, efavirenz, felbamate, griseofulvin, oxcarbazepine, phenytoin, rifampin, rifabutin, rufinamide, topiramate, products containing St. John’s worta, and certain protease inhibitors (see separate section on protease inhibitors below).
Colesevelam
Clinical effect | - Concomitant use of COCs with colesevelam significantly decreases systemic exposure of ethinyl estradiol [see Clinical Pharmacology (12.3)]. - Decreased exposure of the estrogen component of COCs may potentially reduce contraceptive efficacy or result in an increase in breakthrough bleeding, depending on the strength of ethinyl estradiol in the COC.
Prevention or management | Administer 4 or more hours apart to attenuate this drug interaction.

a Induction potency of St. John’s wort may vary widely based on preparation.

Substances increasing the systemic exposure of COCs:

Co-administration of atorvastatin or rosuvastatin and certain COCs containing ethinyl estradiol (EE) increase AUC values for EE by approximately 20-25%. Ascorbic acid and acetaminophen may increase systemic exposure of EE possibly by inhibition of conjugation. CYP3A4 inhibitors such as itraconazole, voriconazole, fluconazole, grapefruit juice, or ketoconazole may increase systemic exposure of estrogen and/or progestin component of COCs.

Human immunodeficiency virus (HIV)/ Hepatitis C virus (HCV) protease inhibitors and non-nucleoside reverse transcriptase inhibitors:

Significant decreases in systemic exposure of the estrogen and/or progestin have been noted when COCs are co-administered with some HIV protease inhibitors (e.g., nelfinavir, ritonavir, darunavir/ritonavir, (fos)amprenavir/ritonavir, lopinavir/ritonavir, and tipranavir/ritonavir] or some HCV protease inhibitors (e.g. boceprevir and telaprevir) and some non-nucleosidase reverse transcriptase inhibitors (e.g. nevirapine).

In contrast, significant increases in systemic exposure of the estrogen and/or progestin have been noted when COCs are co-administered with certain other HIV protease inhibitors (e.g. indinavir and atazanavir/ritonavir) and with other non-nucleoside reverse transcriptase inhibitors (e.g. etravirine).

7.2 Effects of Combined Oral Contraceptives on Other Drugs

Table 6 provides significant drug interaction information for drugs co-administered with JOLESSA.

Table 6: Significant Drug Interaction Information for Drugs Co-Administered With COCs

Lamotrigine
Clinical effect | - Concomitant use of COCs with lamotrigine may significantly decrease systemic exposure of lamotrigine due to induction of lamotrigine glucuronidation [See Clinical Pharmacology (12.3)]. - Decreased systemic exposure of lamotrigine may reduce seizure control.
Prevention or management | Dose adjustment may be necessary. Consult the approved product labeling for lamotrigine.
Thyroid Hormone Replacement Therapy or Corticosteroid Replacement Therapy
Clinical effect | Concomitant use of COCs with thyroid hormone replacement therapy or corticosteroid replacement therapy may increase systemic exposure of thyroid-binding and cortisol-binding globulin [see Warnings and Precautions (5.12)].
Prevention or management | The dose of replacement thyroid hormone or cortisol therapy may need to be increased. Consult the approved product labeling for the therapy in use [see Warnings and Precautions (5.12)].
Other Drugs
Clinical effect | Concomitant use of COCs may decrease systemic exposure of acetaminophen, morphine, salicylic acid, and temazepam. Concomitant use with ethinyl estradiol-containing COCs may increase systemic exposure of other drugs (e.g., cyclosporine, prednisolone, theophylline, tizanidine, and voriconazole).
Prevention or management | The dosage of drugs that can be affected by this interaction may need to be increased. Consult the approved product labeling for the concomitantly used drug.

7.3 Concomitant Use with Hepatitis C Virus (HCV) Combination Therapy – Liver Enzyme Elevation

Co-administration of JOLESSA with HCV drug combinations containing ombitasvir/paritaprevir/ritonavir, with or without dasabuvir is contraindicated due to potential for ALT elevations [see Warnings and Precautions (5.3)]. Co-administration of JOLESSA and glecaprevir/pibrentasvir is not recommended due to potential for ALT elevations.

7.4 Effect on Laboratory Tests

The use of COCs may influence the results of certain laboratory tests, such as coagulation factors, lipids, glucose tolerance, and binding proteins.

8 USE IN SPECIFIC POPULATIONS

8.1 Pregnancy

Risk Summary

There is no use for contraception in pregnancy; therefore, JOLESSA should be discontinued during pregnancy. Epidemiologic studies and meta-analyses have not found an increased risk of genital or non-genital birth defects (including cardiac anomalies and limb-reduction defects) following exposure to COCs before conception or during early pregnancy.

In the U.S. general population, the estimated background risk of major birth defects and miscarriage in clinically recognized pregnancies is 2 to 4 percent and 15 to 20 percent, respectively.

8.2 Lactation

Risk Summary

Contraceptive hormones and/or metabolites are present in human milk. COCs can reduce milk production in breastfeeding females. This reduction can occur at any time but is less likely to occur once breastfeeding is well-established. When possible, advise the nursing female to use other methods of contraception until she discontinues breastfeeding [see Dosage and Administration (2.1)]. The developmental and health benefits of breastfeeding should be considered along with the mother’s clinical need for JOLESSA and any potential adverse effects on the breastfed child from JOLESSA or the underlying maternal condition.

8.4 Pediatric Use

Safety and efficacy of JOLESSA have been established in women of reproductive age. Efficacy is expected to be the same for postpubertal adolescents under the age of 18 as for users 18 years and older. Use of JOLESSA before menarche is not indicated.

8.5 Geriatric Use

JOLESSA has not been studied in postmenopausal women and is not indicated in this population.

8.6 Hepatic Impairment

The pharmacokinetics of JOLESSA have not been studied in subjects with hepatic impairment. However, COCs may be poorly metabolized in patients with hepatic impairment. JOLESSA is contraindicated in females with acute hepatitis or severe decompensated cirrhosis [see Contraindications (4) and Warnings and Precautions (5.2)].

10 OVERDOSAGE

There have been no reports of serious ill effects from overdose of oral contraceptives, including ingestion by children. Overdosage may cause withdrawal bleeding in females and nausea.

11 DESCRIPTION

JOLESSA (levonorgestrel and ethinyl estradiol tablets) is an extended-cycle combination oral contraceptive consisting of 84 pink active tablets each containing 0.15 mg of levonorgestrel, a synthetic progestin and 0.03 mg of ethinyl estradiol, an estrogen, and 7 white inert tablets (without hormones).

The structural formulas for the active components are:

Levonorgestrel

C21H28O2 MW: 312.4

Levonorgestrel is chemically 18,19-Dinorpregn-4-en-20-yn-3-one, 13-ethyl-17-hydroxy-, (17α)-, (-)-.

Ethinyl Estradiol

C20H24O2 MW: 296.4

Ethinyl Estradiol is 19-Norpregna-1,3,5(10)-trien-20-yne-3,17-diol, (17α)-.

- Each pink active tablet contains the following inactive ingredients: anhydrous lactose NF, FD&C blue no. 1, FD&C red no. 40, hydroxypropyl methylcellulose USP, microcrystalline cellulose NF, polyethylene glycol NF, magnesium stearate NF, polysorbate 80 NF, and titanium dioxide USP.
- Each white inert tablet contains the following inactive ingredients: anhydrous lactose NF, hydroxypropyl methylcellulose USP, microcrystalline cellulose NF, and magnesium stearate NF.

12 CLINICAL PHARMACOLOGY

12.1 Mechanism of Action

COCs prevent pregnancy primarily by suppressing ovulation.

12.2 Pharmacodynamics

No specific pharmacodynamic studies were conducted with JOLESSA.

12.3 Pharmacokinetics

Absorption

No specific investigation of the absolute bioavailability of JOLESSA in humans has been conducted. However, literature indicates that levonorgestrel is rapidly and completely absorbed after oral administration (bioavailability nearly 100%) and is not subject to first-pass metabolism. EE is rapidly and almost completely absorbed from the gastrointestinal tract but, due to first-pass metabolism in gut mucosa and liver, the bioavailability of EE is approximately 43%.

Following continuous dosing with once-daily administration of JOLESSA tablets, plasma concentrations of levonorgestrel and EE reached steady-state within 7 days. The mean plasma pharmacokinetic parameters for JOLESSA under fasting conditions in normal healthy women following once-daily administration of one levonorgestrel/EE combination tablet for 10 days are summarized in Table 7.

Table 7: Mean ±SD Pharmacokinetic Parameters Under Fasting Conditions in Healthy Women Following 10 Days Administration of One Tablet of JOLESSA (n=44)

Analyte | AUC0-24 | Cmax | Cmin | Cavga | Tmax
Levonorgestrel | 54.6 ± 16.5; ng*hr/mL | 5.0 ± 1.5 ng/mL | 1.6 ± 0.5; ng/mL | 2.3 ± 0.7; ng/mL | 1.4 ± 0.7 hours
Ethinyl estradiol | 935.5 ± 346.9; pg*hr/mL | 106.1 ± 41.2; pg/mL | 18.5 ± 9.4 pg/mL | 38.9 ± 14.4 pg/mL | 1.6 ± 0.6; hours

a Cavg = AUC0-24/24

Food Effect

The effect of food on the rate and the extent of levonorgestrel and EE absorption following oral administration of JOLESSA has not been evaluated.

Distribution

The apparent volume of distribution of levonorgestrel and EE are reported to be approximately 1.8 L/kg and 4.3 L/kg, respectively. Levonorgestrel is about 97.5 - 99% protein-bound, principally to sex hormone binding globulin (SHBG) and, to a lesser extent, serum albumin. EE is about 95 - 97% bound to serum albumin. EE does not bind to SHBG, but induces SHBG synthesis, which leads to decreased levonorgestrel clearance. Following repeated daily dosing of levonorgestrel/EE oral contraceptives, levonorgestrel plasma concentrations accumulate more than predicted based on single-dose pharmacokinetics, due in part, to increased SHBG levels that are induced by EE, and a possible reduction in hepatic metabolic capacity.

Metabolism

Following absorption, levonorgestrel is conjugated at the 17β-OH position to form sulfate and to a lesser extent, glucuronide conjugates in plasma. Significant amounts of conjugated and unconjugated 3α,5β-tetrahydrolevonorgestrel are also present in plasma, along with much smaller amounts of 3α,5α-tetrahydrolevonorgestrel and 16β-hydroxylevonorgestrel. Levonorgestrel and its phase I metabolites are excreted primarily as glucuronide conjugates. Metabolic clearance rates may differ among individuals by several-fold, and this may account in part for the wide variation observed in levonorgestrel concentrations among users.

First-pass metabolism of EE involves formation of EE-3-sulfate in the gut wall, followed by 2-hydroxylation of a portion of the remaining untransformed EE by hepatic cytochrome P-450 3A4 (CYP3A4). Levels of CYP3A4 vary widely among individuals and can explain the variation in rates of EE hydroxylation. Hydroxylation at the 4-, 6-, and 16- positions may also occur, although to a much lesser extent than 2-hydroxylation. The various hydroxylated metabolites are subject to further methylation and/or conjugation.

Excretion

About 45% of levonorgestrel and its metabolites are excreted in the urine and about 32% are excreted in feces, mostly as glucuronide conjugates. The terminal elimination half-life for levonorgestrel after a single dose of JOLESSA was about 30 hours.

EE is excreted in the urine and feces as glucuronide and sulfate conjugates, and it undergoes enterohepatic recirculation. The terminal elimination half-life of EE after a single dose of JOLESSA was found to be about 15 hours.

13 NONCLINICAL TOXICOLOGY

13.1 Carcinogenesis, Mutagenesis, Impairment of Fertility

See Warnings and Precautions (5.2, 5.11).

14 CLINICAL STUDIES

In a 12-month, multicenter, randomized, open-label clinical trial, 456 women aged 18-40 were studied to assess the safety and efficacy of JOLESSA, completing 809 91-day cycles of exposure. The racial demographic of those enrolled was: Caucasian (77%), African-American (11%), Hispanic (7%), Asian (2%), and Other (3%). There were no exclusions for body mass index (BMI) or weight. The weight range of those women treated was 84 to 304 pounds, with a mean weight of 157 pounds and a median weight of 147 pounds. Among the women in the trial, 63% were current or recent hormonal contraceptive users, 29% were prior users (who had used hormonal contraceptives in the past but not in the 6 months prior to enrollment), and 8% were new starts.

The pregnancy rate (Pearl Index [PI]) in the 397 women aged 18-35 years was 1.98 pregnancies per 100 women-years of use (95% CI: 0.54 to 5.03), based on 4 pregnancies that occurred after the onset of treatment and within 14 days after the last combination pill. Cycles in which conception did not occur, but which included the use of backup contraception, were not included in the calculation of the PI.

16 HOW SUPPLIED/STORAGE AND HANDLING

How Supplied

JOLESSA (levonorgestrel and ethinyl estradiol tablets) are available as round, film-coated, biconvex, unscored tablets with a debossed stylized b on one side, packaged in Extended-Cycle Tablet Dispensers, each containing a 13-week supply of tablets in the following order:

- 84 pink tablets, each containing 0.15 mg of levonorgestrel and 0.03 mg ethinyl estradiol: debossed with 992 on the other side
- 7 white inert tablets debossed with 208 on the other side

Box of 3 Extended-Cycle Tablet Dispensers NDC 0555-9123-66

Storage and Handling

- Store at 20°C to 25°C (68°F to 77°F); excursions permitted to 15ºC to 30ºC (59ºF to 86ºF) [See USP Controlled Room Temperature].
- Protect from light.

17 PATIENT COUNSELING INFORMATION

Advise the patient to read the FDA-approved patient labeling (Patient Information and Instructions for Use).

Cigarette Smoking

Cigarette smoking increases the risk of serious cardiovascular events from COC use. Women who are over 35 years old and smoke should not use JOLESSA [see Boxed Warning and Warnings and Precautions (5.1)].

Venous Thromboembolism

The increased risk of VTE compared to non-users of COCs is greatest after initially starting a COC or restarting (following a 4-week or greater pill-free interval) the same or a different COC [see Warnings and Precautions (5.1)].

Use During Pregnancy

Instruct females to stop further intake of JOLESSA if pregnancy is confirmed during treatment.

Sexually Transmitted Infections

JOLESSA does not protect against HIV-infection (AIDS) and other sexually transmitted infections.

Dosing and Missed Pill Instructions

- Patients should take one tablet daily by mouth at the same time every day [see Dosage and Administration (2.1)].
- Instruct patients what to do in the event tablets are missed. See “What should I do if I miss any JOLESSA pills” section in FDA-approved Instructions for Use [see Dosage and Administration (2.3)].

Need for Additional Contraception

- Postpartum females who start JOLESSA who have not yet had a period when they start JOLESSA need to use an additional method of contraception until they have taken a pink tablet for 7 consecutive days [see Dosage and Administration (2.1)].
- There is a need for a backup or alternative method of contraception when enzyme inducers are used with JOLESSA [see Drug Interactions (7.1)].

Lactation

JOLESSA may reduce breast milk production. This is less likely to occur if breastfeeding is well established. When possible, nursing women should use other methods of contraception until they have discontinued breastfeeding [see Use in Specific Populations (8.2)].

Amenorrhea and Possible Symptoms of Pregnancy

Amenorrhea may occur. Because women using JOLESSA will likely have scheduled bleeding only 4 times per year, advise women to contact their health care provider in the event of amenorrhea with symptoms of pregnancy such as morning sickness or unusual breast tenderness [see Warnings and Precautions (5.9)].

Depression

Depressed mood and depression may occur. Women should contact their healthcare provider if mood changes and depressive symptoms occur, including shortly after initiating the treatment [see Warnings and Precautions (5.10)].

Manufactured for:
Teva Pharmaceuticals
Parsippany, NJ 07054

JOL-005

Revised: 10/2024

© 2024 Teva Pharmaceuticals, Inc.

FDA-approved Patient Labeling

PATIENT INFORMATION

JOLESSA® [joe les’ a]

(levonorgestrel and ethinyl estradiol tablets)

WARNING TO WOMEN WHO SMOKE

Do not use JOLESSA if you smoke cigarettes and are over 35 years old. Smoking increases your risk of serious cardiovascular side effects from birth control pills, including death from heart attack, blood clots or stroke. This risk increases with age and the number of cigarettes you smoke.

What is the most important information I should know about JOLESSA?

Do not use JOLESSA if you smoke cigarettes and are over 35 years old. Smoking increases your risk of serious cardiovascular side effects from birth control pills, including death from heart attack, blood clots or stroke. This risk increases with age and the number of cigarettes you smoke.

What is JOLESSA?

JOLESSA is a birth control pill (oral contraceptive) used by women to prevent pregnancy. It contains two female hormones, an estrogen called ethinyl estradiol, and a progestin called levonorgestrel. JOLESSA does not protect against HIV infections (AIDS) and other sexually transmitted infections.

How does JOLESSA work for contraception?

Your chance of getting pregnant depends on how well you follow the directions for taking your birth control pills. The better you follow the directions, the less chance you have of getting pregnant.

Based on the results of clinical studies, about 1 to 5 out of 100 women may get pregnant during the first year they use JOLESSA.

The following chart shows the chance of getting pregnant for women who use different methods of birth control. Each box on the chart contains a list of birth control methods that are similar in effectiveness. The most effective methods are at the top of the chart. The box on the bottom of the chart shows the chance of getting pregnant for women who do not use birth control and are trying to get pregnant.

Who should not take JOLESSA?

Do not take JOLESSA if you:

- smoke and are over 35 years of age
- have or had blood clots in your arms, legs, lungs, or eyes
- had a stroke
- had a heart attack
- have certain heart valve problems or heart rhythm abnormalities that can cause blood clots to form in the heart
- have or had a problem with your blood that makes it clot more than normal
- have high blood pressure that cannot be controlled by medicine or have high blood pressure with blood vessels problems
- have diabetes
  - and are over the age of 35
  - with high blood pressure
  - with kidney, eye, nerve, or blood vessel damage
  - for more than 20 years
- have certain kinds of severe migraine headaches with aura, numbness, weakness or changes in vision, or any migraine headaches if you are over 35 years of age
- have or had breast cancer
- have liver problems, including liver tumors
- have any unexplained vaginal bleeding
- take any Hepatitis C drug combination containing ombitasvir/paritaprevir/ritonavir, with or without dasabuvir. This may increase levels of the liver enzyme “alanine aminotransferase” (ALT) in the blood.

If any of these conditions happen to you while you are taking JOLESSA, stop taking JOLESSA right away and talk to your healthcare provider. Use non-hormonal contraception when you stop taking JOLESSA.

What should I tell my healthcare provider before taking JOLESSA?

Tell your healthcare provider if you:

- are pregnant or think you may be pregnant
- are scheduled for surgery. JOLESSA may increase your risk of blood clots after surgery. You should stop taking JOLESSA at least 4 weeks before you have surgery and not restart JOLESSA until at least 2 weeks after your surgery.
- are depressed now or have been depressed in the past
- had yellowing of your skin or eyes (jaundice) caused by pregnancy (cholestasis of pregnancy)
- are breastfeeding or plan to breastfeed. JOLESSA may decrease the amount of breast milk you make. A small amount of the hormones in JOLESSA may pass into your breast milk. Talk to your healthcare provider about the best birth control method for you while breastfeeding.

Tell your healthcare provider if you have ever had any of the conditions listed in, “Who should not take JOLESSA” above. Your healthcare provider may recommend another method of birth control.

Tell your healthcare provider about all the medicines you take, including prescription and over-the-counter medicines, vitamins and herbal supplements.

JOLESSA may affect the way other medicines work, and other medicines may affect how well JOLESSA works.

Some medicines and herbal products may make birth control pills less effective, including:

- barbiturates
- bosentan
- carbamazepine
- felbamate
- griseofulvin
- oxcarbazepine
- phenytoin
- rifampin
- St. John’s wort
- topiramate

Use a backup or alternative birth control method when you take medicines that may make birth control pills less effective.

Birth control pills may interact with lamotrigine, an anticonvulsant used for epilepsy. This may increase the risk of seizures, so your physician may need to adjust the dose of lamotrigine.

Women on thyroid hormone replacement therapy may need increased doses of thyroid hormone.

Know the medicines you take. Keep a list of them to show your healthcare provider and pharmacist when you get a new medicine.

How should I take JOLESSA?

Read the Instructions for Use at the end of this Patient Information.

What are the most serious risks of taking JOLESSA?

Like pregnancy, JOLESSA may cause serious side effects, including blood clots in your lungs, heart attack, or a stroke that may lead to death. Some other examples of serious blood clots include blood clots in the legs or eyes. Serious blood clots can happen especially if you smoke, are obese, or are older than 35 years of age. Serious blood clots are more likely to happen when you:

- first start taking birth control pills
- restart the same or different birth control pills after not using them for a month or more

Call your healthcare provider or go to a hospital emergency room right away if you have:

- leg pain that will not go away
- sudden severe shortness of breath
- sudden change in vision or blindness
- chest pain
- a sudden, severe headache unlike your usual headaches
- weakness or numbness in your arm or leg
- trouble speaking
- yellowing of your skin or eyes

Other serious side effects include:

- liver problems, including:
  - rare liver tumors
  - jaundice (cholestasis), especially if you previously had cholestasis of pregnancy.

- high blood pressure. You should see your healthcare provider to check your blood pressure regularly.
- gallbladder problems
- changes in the sugar and fat (cholesterol and triglycerides) levels in your blood
- new or worsening headaches including migraine headaches
- irregular or unusual vaginal bleeding and spotting between your menstrual periods, especially during the first 3 months of taking JOLESSA.
- depression, especially if you have had depression in the past. Call your healthcare provider immediately if you have any thoughts of harming yourself.
- possible cancer in your breast and cervix
- swelling of your skin especially around your mouth, eyes, and in your throat (angioedema). Call your healthcare provider if you have a swollen face, lips, mouth tongue or throat, which may lead to difficulty swallowing or breathing. Your chance of having angioedema is higher is you have a history of angioedema.
- dark patches of skin around your forehead, nose, cheeks and around your mouth, especially during pregnancy (chloasma). Women who tend to get chloasma should avoid spending a long time in sunlight, tanning booths, and under sun lamps while taking JOLESSA. Use sunscreen if you have to be in the sunlight.

What are the most common side effects of JOLESSA?

- headache (migraine)
- heavier or longer periods, pain with periods
- nausea
- acne
- breast tenderness
- increase in weight

These are not all the possible side effects of JOLESSA. For more information, ask your healthcare provider or pharmacist. You may report side effects to the FDA at 1-800-FDA-1088.

What else should I know about taking JOLESSA?

- If you are scheduled for any lab tests, tell your healthcare provider you are taking JOLESSA. Certain blood tests may be affected by JOLESSA.
- Do not skip any pills, even if you do not have sex often.
- Birth control pills should not be taken during pregnancy. However, birth control pills taken by accident during pregnancy are not known to cause birth defects.
- You should stop JOLESSA at least four weeks before you have major surgery and not restart it for at least two weeks after the surgery, due to an increased risk of blood clots.
- If you are breastfeeding, consider another birth control method until you are ready to stop breastfeeding. Birth control pills that contain estrogen, like JOLESSA, may decrease the amount of milk you make. A small amount of the pill's hormones pass into breast milk, but this has not caused harmful effects in breastfeeding infants.
- If you have vomiting or diarrhea, your birth control pills may not work as well. Use another birth control method, like condoms or a spermicide, until you check with your healthcare provider.

How should I store JOLESSA?

- Store JOLESSA at room temperature between 68°F to 77°F (20°C to 25°C). Protect from light.
- Keep JOLESSA and all medicines out of the reach of children.

General information about the safe and effective use of JOLESSA

Medicines are sometimes prescribed for purposes other than those listed in a Patient Information leaflet. Do not use JOLESSA for a condition for which it was not prescribed. Do not give JOLESSA to other people, even if they have the same symptoms that you have.

This Patient Information summarizes the most important information about JOLESSA. You can ask your pharmacist or healthcare provider for information about JOLESSA that is written for health professionals.

For more information, call 1-888-483-8279 (1-888-4Teva-RX).

Do birth control pills cause cancer?

It is not known if hormonal birth control pills cause breast cancer. Some studies, but not all, suggest that there could be a slight increase in the risk of breast cancer among current users with longer duration of use.

If you have breast cancer now, or have had it in the past, do not use hormonal birth control because some breast cancers are sensitive to hormones. Women who use birth control pills may have a slightly higher chance of getting cervical cancer. However, this may be due to other reasons such as having more sexual partners.

What if I want to become pregnant?

You may stop taking the pill whenever you wish. Consider a visit with your healthcare provider for a pre-pregnancy checkup before you stop taking the pill.

What should I know about my period when taking JOLESSA?

When you take JOLESSA, which has a 91-day extended dosing cycle, you should have 4 scheduled periods a year (bleeding when you are taking the 7 white pills). However, you will probably have more bleeding or spotting between your scheduled periods than if you were using a birth control pill with a 28-day dosing cycle. During the first JOLESSA 91-day treatment cycle, about 1 in 3 women may have 20 or more days of unplanned bleeding or spotting. This bleeding or spotting tends to decrease with time. Do not stop taking JOLESSA because of this bleeding or spotting. If the spotting continues for more than 7 days in a row or if the bleeding is heavy, call your healthcare provider.

What if I miss my scheduled period when taking JOLESSA?

You should consider the possibility that you are pregnant if you miss your scheduled period (no bleeding on the days that you are taking white pills). Since scheduled periods are less frequent when you are taking JOLESSA, notify your healthcare provider that you have missed your period and that you are taking JOLESSA. Also notify your healthcare provider if you have symptoms of pregnancy such as morning sickness or unusual breast tenderness. It is important that your healthcare provider evaluates you to determine if you are pregnant. Stop taking JOLESSA if it is determined that you are pregnant.

What are the ingredients in JOLESSA?

Active ingredients: Each pink pill contains levonorgestrel and ethinyl estradiol.

Inactive ingredients:

Pink pills: anhydrous lactose NF, FD&C blue no. 1, FD&C red no. 40, hydroxypropyl methylcellulose USP, microcrystalline cellulose NF, polyethylene glycol NF, magnesium stearate NF, polysorbate 80 NF, and titanium dioxide USP.

White pills: anhydrous lactose NF, hydroxypropyl methylcellulose USP, microcrystalline cellulose NF, and magnesium stearate NF.

INSTRUCTIONS FOR USE

JOLESSA® [joe les’ a]

(levonorgestrel and ethinyl estradiol tablets)

Important information about taking JOLESSA

- Take 1 pill every day at the same time. Take the pills in the order directed on your pill dispenser.
- Do not skip your pills, even if you do not have sex often. If you miss pills (including starting the pack late) you could get pregnant. The more pills you miss, the more likely you are to get pregnant.
- If you have trouble remembering to take JOLESSA, talk to your healthcare provider.
- When you first start taking JOLESSA, spotting or light bleeding in between your periods may occur. Contact your healthcare provider if this does not go away after a few months.
- You may feel sick to your stomach (nauseous), especially during the first few months of taking JOLESSA. If you feel sick to your stomach, do not stop taking the pill. The problem will usually go away. If your nausea does not go away, call your healthcare provider.
- Missing pills can also cause spotting or light bleeding, even when you take the missed pills later. On the days you take 2 pills to make up for missed pills (see, “What should I do if I miss any JOLESSA pills?” below), you could also feel a little sick to your stomach.
- It is not uncommon to miss a period. However, if you miss a period and have not taken JOLESSA according to directions, or feel like you may be pregnant, call your healthcare provider. If you have a positive pregnancy test, you should stop taking JOLESSA.
- If you have vomiting or diarrhea within 3-4 hours of taking a pink pill, take another pink pill as soon as possible. Continue taking one pill a day until the 91-day course is finished.
- If you have vomiting or diarrhea for more than 1 day, your birth control pills may not work as well. Use an additional birth control method, like condoms or spermicide, until you check with your healthcare provider.
- Stop taking JOLESSA at least 4 weeks before you have major surgery and do not restart after the surgery without asking your healthcare provider. Be sure to use other forms of contraception (like condoms or spermicide) during this time period.

Before you start taking JOLESSA:

- Decide what time of day you want to take your pill. It is important to take it at about the same time every day.
- Look at your Extended-Cycle Tablet Dispenser. Your Tablet Dispenser consists of 3 trays with cards that hold 91 individually sealed pills (a 13-week or 91-day cycle). The 91 pills consist of 84 pink and 7 white pills. The cards in trays 1 and 2 each contain 28 pink pills (4 rows of 7 pills). See Figure A. The card in tray 3 contains 35 pills consisting of 28 pink pills (4 rows of 7 pills) and 7 white pills (1 row of 7 pills). See Figure B.

Figure A

Figure B

- Also find:
  - Where on the first tray in the pack to start taking pills (upper left corner) and
  - In what order to take the pills (follow the weeks)
- Be sure you have ready at all times another kind of birth control (such as condoms or spermicide), to use as a backup in case you miss pills.

When should I start taking JOLESSA?

If you start taking JOLESSA and you have not used a hormonal birth control method before:

- Take the first pink pill on the Sunday after your period starts, even if you are still bleeding. If your period begins on Sunday, start the first pink pill that same day.
- Use another method of birth control (such as condoms or spermicide) as a backup method if you have sex anytime from the Sunday you start your first pink pill until the next Sunday (first 7 days).

If you have recently given birth and have not yet had a period, use another method of birth control if you have sex (such as condoms and spermicide) as a backup method until you have taken JOLESSA for 7 days.

If you start taking JOLESSA and you are switching from another birth control pill:

- Start your new JOLESSA pack on the same day that you would start the next pack of your previous birth control method.
- Do not continue taking the pills from your previous birth control pack.

If you start taking JOLESSA and previously used a vaginal ring:

- Start using JOLESSA on the day you would have reapplied the next ring.

If you start taking JOLESSA and previously used a transdermal patch:

- Start using JOLESSA on the day you would have started a new cycle (first patch application).

If you start taking JOLESSA and you are switching from a progestin-only method such as an implant or injection:

- Start taking JOLESSA on the day of removal of your implant, or on the day when you would have had your next injection.

If you start taking JOLESSA and you are switching from an intrauterine device or system (IUD or IUS):

- Start taking JOLESSA on the day of removal of your IUD or IUS.
- You do not need backup contraception if your IUD or IUS is removed on the first day (Day 1) of your period. If your IUD or IUS is removed on any other day, use non-hormonal backup contraception such as condoms or spermicide for the first 7 days that you take JOLESSA.

Keep a calendar to track your period: If this is the first time you are taking birth control pills, read, “When should I start taking JOLESSA?” above. Follow these instructions for a Sunday Start.

Instructions for using your JOLESSA Extended-Cycle Tablet Dispenser:

Sunday Start:

- Take pill 1 on the Sunday after your period starts. To remove your pill from the dispenser, press the pill through the hole in the bottom of the dispenser. See Figure C.

Figure C

- If your period starts on a Sunday, take pill “1” that same day.
- Take 1 pill at about the same time every day until you have taken the last pill in the tablet dispenser.
- After taking the last white pill on Day 91 from the pill dispenser, start taking the first pink pill from a new Extended-Cycle Tablet Dispenser on the very next day (this should be a Sunday). Take the first pill in the new pack whether or not you are having your period.
- Use non-hormonal backup contraception such as condoms or spermicide for the first 7 days of the first cycle that you take JOLESSA.

What should I do if I miss any JOLESSA pills?

If you miss 1 pink pill, follow these steps:

- Take it as soon as you remember. Take the next pill at your regular time. This means you may take 2 pills in 1 day.
- Then continue taking 1 pill every day until you finish the pack.
- You do not need to use a backup birth control method if you have sex.

If you miss 2 pink pills in a row, follow these steps:

- Take 2 pills on the day you remember and 2 pills the next day.
- Then continue to take 1 pill every day until you finish the pack.
- You could become pregnant if you have sex in the 7 days after you miss two pills. You must use a non-hormonal birth control method (such as a condom or spermicide) as a backup if you have sex during the first 7 days after you restart your pills.

If you miss 3 or more pink pills in a row, follow these steps:

- Do not take the missed pills. Keep taking 1 pill every day until you have completed all of the remaining pills in the pack. For example, if you start taking the pill on Thursday, take the pill under “Thursday” and do not take the missed pills. You may have bleeding during the week following the missed pills.
- You could become pregnant if you have sex during the days of missed pills or during the first 7 days after restarting your pills. You must use a non-hormonal birth control method (such as a condom or spermicide) as a backup when you miss pills and for the first 7 days after you restart your pills. If you do not have your period when you are taking the white pills, call your healthcare provider because you may be pregnant.

If you miss any of the 7 white pills:

- Throw away the missed pills.
- Keep taking the scheduled pills until the pack is finished.
- You do not need a backup method of birth control.

Finally, if you are still not sure what to do about the pills you have missed

- Use a backup method anytime you have sex.
- Keep taking one pill each day until you contact your healthcare provider.

If you have any questions or are unsure about the information in this leaflet, call your healthcare provider.

Manufactured for:
Teva Pharmaceuticals
Parsippany, NJ 07054

This Patient Information and Instructions for Use have been approved by the U.S. Food and Drug Administration.

JOLPL-005

Revised: 10/2024

©2024 Teva Pharmaceuticals, Inc.

Package/Label Display Panel, Part 1 of 2

NDC 0555-9123-66

Jolessa®

(levonorgestrel/ethinyl estradiol tablets)

0.15 mg/0.03 mg

Contains 3 Extended-Cycle Tablet Dispensers, each containing 91 tablets: 84 pink tablets, each containing 0.15 mg levonorgestrel with 0.03 mg ethinyl estradiol, and 7 white inert tablets.

Rx only

3 Extended-Cycle Tablet Dispensers,

91 Tablets Each

91 DAY REGIMEN

TEVA